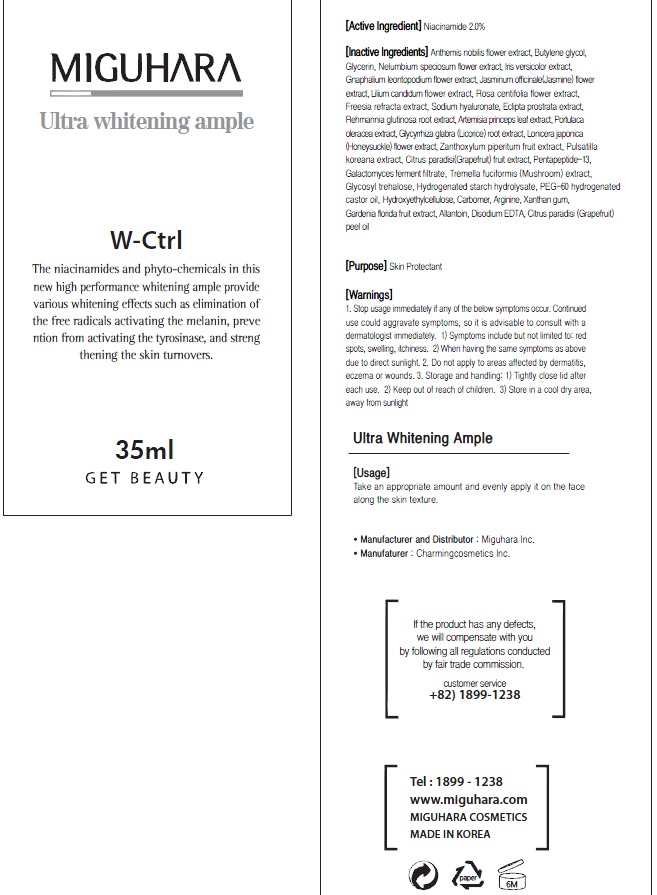 DRUG LABEL: Ultra Whitening Ample
NDC: 70380-320 | Form: CREAM
Manufacturer: MIGUHARA
Category: otc | Type: HUMAN OTC DRUG LABEL
Date: 20160224

ACTIVE INGREDIENTS: Niacinamide 0.7 g/35 mL
INACTIVE INGREDIENTS: CHAMAEMELUM NOBILE FLOWER; Butylene glycol

ACTIVE INGREDIENT

Active Ingredient: Niacinamide 2.0%

INACTIVE INGREDIENT

Inactive Ingredients: Anthemis nobilis flower extract, Butylene glycol, Glycerin, Nelumbium speciosum flower extract, Iris versicolor extract, Gnaphalium leontopodium flower extract, Jasminum officinale(Jasmine) flower extract, Lilium candidum flower extract, Rosa centifolia flower extract, Freesia refracta extract, Sodium hyaluronate, Eclipta prostrata extract, Rehmannia glutinosa root extract, Artemisia princeps leaf extract, Portulaca oleracea extract, Glycyrrhiza glabra (Licorice) root extract, Lonicera japonica(Honeysuckle) flower extract, Zanthoxylum piperitum fruit extract, Pulsatilla koreana extract, Citrus paradisi(Grapefruit) fruit extract, Pentapeptide-13, Galactomyces ferment filtrate, Tremella fuciformis (Mushroom) extract, Glycosyl trehalose, Hydrogenated starch hydrolysate, PEG-60 hydrogenated castor oil, Hydroxyethylcellulose, Carbomer, Arginine, Xanthan gum, Gardenia florida fruit extract, Allantoin, Disodium EDTA, Citrus paradisi (Grapefruit) peel oil

PURPOSE

Purpose: Skin Protectant

WARNINGS

1. Stop usage immediately if any of the below symptoms occur. Continued use could aggravate symptoms, so it is advisable to consult with a dermatologist immediately. 1) Symptoms include but not limited to: red spots, swelling, itchiness. 2) When having the same symptoms as above due to direct sunlight. 2. Do not apply to areas affected by dermatitis, eczema or wounds. 3. Storage and handling: 1) Tightly close lid after each use. 2 Keep out of reach of children 3) Store in a cool dry area, away from sunlight

KEEP OUT OF REACH OF CHILDREN

Usage

Usage: Take an appropriate amount and evenly apply it on the face along the skin texture.

Usage

Usage: Take an appropriate amount and evenly apply it on the face along the skin texture.